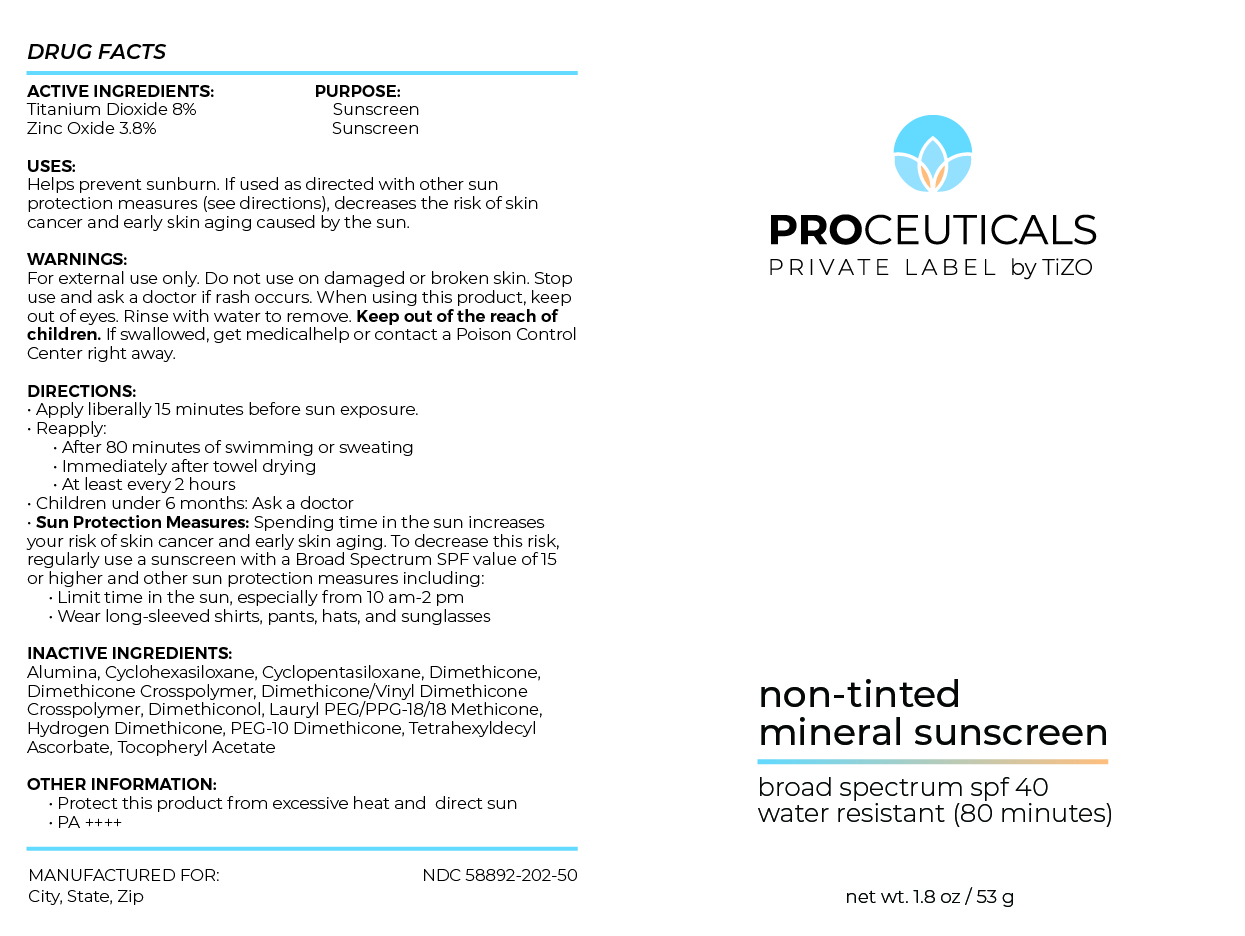 DRUG LABEL: PROCEUTICALS PRIVATE LABEL by TiZO non-tinted mineral sunscreen
NDC: 58892-202 | Form: CREAM
Manufacturer: Fallien Cosmeceuticals, LTD
Category: otc | Type: HUMAN OTC DRUG LABEL
Date: 20240710

ACTIVE INGREDIENTS: ZINC OXIDE 38 mg/1 g; TITANIUM DIOXIDE 80 mg/1 g
INACTIVE INGREDIENTS: LAURYL PEG/PPG-18/18 METHICONE; TETRAHEXYLDECYL ASCORBATE; .ALPHA.-TOCOPHEROL ACETATE; ALUMINUM HYDROXIDE; DIMETHICONE 20; DIMETHICONE CROSSPOLYMER (450000 MPA.S AT 12% IN CYCLOPENTASILOXANE); DIMETHICONE/VINYL DIMETHICONE CROSSPOLYMER (SOFT PARTICLE); HYDROGEN DIMETHICONE (20 CST); CYCLOMETHICONE 6; CYCLOMETHICONE 5; PEG-10 DIMETHICONE (600 CST); DIMETHICONOL (2000 CST)

ACTIVE INGREDIENTS:
Titanium Dioxide 8%
Zinc Oxide 3.8%

PURPOSE:Sunscreen

DIRECTIONS:
• Apply liberally 15 minutes before sun exposure.
• Reapply:
• After 40 minutes of swimming or sweating
• Immediately after towel drying
• At least every 2 hours
• Children under 6 months: Ask a doctor
• Sun Protection Measures: Spending time in the sun increases
your risk of skin cancer and early skin aging. To decrease this risk,
regularly use a sunscreen with a Broad Spectrum SPF value of 15 or
higher and other sun protection measures including:
• Limit time in the sun, especially from 10 am-2 pm
• Wear long-sleeved shirts, pants, hats, and sunglasses

INACTIVE INGREDIENTS:

Alumina, Cyclohexasiloxane, Cyclopentasiloxane, Dimethicone,
Dimethicone Crosspolymer, Dimethicone/Vinyl Dimethicone
Crosspolymer, Dimethiconol, Lauryl PEG/PPG-18/18 Methicone,
Hydrogen Dimethicone, PEG-10 Dimethicone, Tetrahexyldecyl
Ascorbate, Tocopheryl Acetate

OTHER INFORMATION:
• Protect this product from excessive heat and direct sun
• PA ++++

WARNINGS:
For external use only. Do not use on damaged or broken skin. Stop
use and ask a doctor if rash occurs. When using this product, keep
out of eyes. Rinse with water to remove. Keep out of the reach of
children. If swallowed, get medical help or contact a Poison Control
Center right away.

Keep out of the reach of
children.

DOSAGE AND ADMINISTRATION

Helps prevent sunburn. If used as directed with other sun
protection measures (see Directions), decreases the risk of skin
cancer and early skin aging caused by the sun.

Apply liberally 15 minutes before sun exposure.

Principal Display Panel – 53 g Bottle Label

Proceuticals

PRIVATE LABEL by TiZO

non-tinted
mineral sunscreen

broad spectrum spf 40
water resistant (80 minutes)

net wt. 1.8 oz / 53 g

Graphic-Untitled